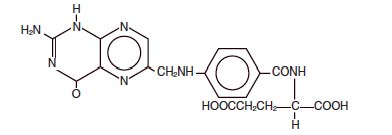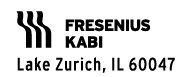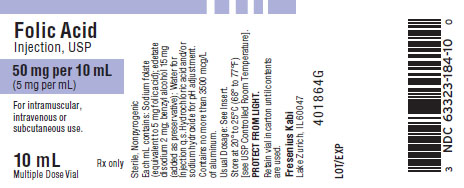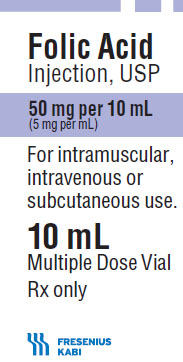 DRUG LABEL: Folic Acid

NDC: 63323-184 | Form: INJECTION, SOLUTION
Manufacturer: Fresenius Kabi USA, LLC
Category: prescription | Type: HUMAN PRESCRIPTION DRUG LABEL
Date: 20241014

ACTIVE INGREDIENTS: FOLIC ACID 5 mg/1 mL
INACTIVE INGREDIENTS: EDETATE SODIUM 2 mg/1 mL; BENZYL ALCOHOL 15 mg/1 mL; HYDROCHLORIC ACID; SODIUM HYDROXIDE

Folic Acid Injection, USP

Rx only

DESCRIPTION:

Folic Acid Injection, USP is a sterile, nonpyrogenic solution of sodium folate (prepared by the addition of sodium hydroxide to folic acid) in Water for Injection intended for intramuscular (IM), intravenous (IV) or subcutaneous (SC) use.

Folic Acid is a complex organic compound present in liver, yeast and other substances, which may be prepared synthetically. It is a yellow or yellowish orange, odorless crystalline powder. It is very slightly soluble in water, insoluble in alcohol, chloroform, ether; readily dissolves in dilute solutions of alkali hydroxides and carbonates. It is chemically designated as: L-Glutamic acid, N-[4-[[(2-amino-1-4-dihydro-4-oxo-6-pteridinyl) methyl] amino]benzoyl]-, and has the following structural formula.

C19H19N7O6 M.W. 441.40

Each mL contains: Sodium folate (equivalent to 5 mg folic acid); edetate disodium 2 mg; benzyl alcohol 15 mg (added as preservative); Water for Injection q.s. Hydrochloric acid and/or sodium hydroxide for pH adjustment (8.0 to 11.0).

CLINICAL PHARMACOLOGY:

In man, an exogenous source of folate is required for nucleoprotein synthesis and maintenance of normal erythropoiesis. Folic acid, whether given by mouth or parenterally, stimulates specifically the production of red blood cells, white blood cells and platelets in persons suffering from certain megaloblastic anemias.

INDICATIONS AND USAGE:

Folic Acid Injection, USP alone is effective in the treatment of megaloblastic anemias due to a deficiency of folic acid as may be seen in tropical or nontropical sprue, in anemias of nutritional origin, pregnancy, infancy or childhood.

WARNINGS:

WARNING: This product contains aluminum that may be toxic. Aluminum may reach toxic levels with prolonged parenteral administration if kidney function is impaired. Premature neonates are particularly at risk because their kidneys are immature, and they require large amounts of calcium and phosphate solutions, which contain aluminum.

Research indicates that patients with impaired kidney function, including premature neonates, who receive parenteral levels of aluminum at greater than 4 to 5 mcg/kg/day accumulate aluminum at levels associated with central nervous system and bone toxicity. Tissue loading may occur at even lower rates of administration.

Folic acid alone is improper therapy in the treatment of pernicious anemia and other megaloblastic anemias where Vitamin B12 is deficient.

This product contains benzyl alcohol. Benzyl alcohol has been reported to be associated with a fatal “Gasping Syndrome” in premature infants.

PRECAUTIONS:

Folic acid in doses above 0.1 mg daily may obscure pernicious anemia in that hematologic remission can occur while neurological manifestations remain progressive.

ADVERSE REACTIONS:

Allergic sensitization has been reported following both oral and parenteral administration of folic acid.

DOSAGE AND ADMINISTRATION:

Parenteral Administration: IM, IV and SC routes may be used if the disease is exceptionally severe or if gastrointestinal absorption may be, or is known to be, impaired.

Usual Therapeutic Dosage— In adults and children (regardless of age): up to 1 mg daily.Resistant cases may require larger doses.

Maintenance Level: When clinical symptoms have subsided and the blood picture has become normal, a maintenance level should be used, i.e., 0.1 mg for infants and up to 0.3 mg for children under four years of age, 0.4 mg for adults and children four or more years of age and 0.8 mg for pregnant and lactating women, per day, but never less than 0.1 mg per day. Patient should be kept under close supervision and adjustment of the maintenance level made if relapse appears imminent.

In the presence of alcoholism, hemolytic anemia, anticonvulsant therapy or chronic infection, the maintenance level may need to be increased.

Parenteral drug products should be inspected visually for particulate matter and discoloration prior to administration, whenever solution and container permit.

HOW SUPPLIED:

Folic Acid Injection, USP 50 mg per 10 mL (5 mg per mL) is available as:

Product No. | NDC No.
18410 | 63323-184-10 | 50 mg per 10 mL (5 mg per mL), 10 mL Multiple Dose, in a flip-top vial packaged individually.
18411 | 63323-184-11 | 50 mg per 10 mL (5 mg per mL), 10 mL Multiple Dose, in a flip-top vial, 10 vials per tray.

Store at 20° to 25°C (68° to 77°F) [see USP Controlled Room Temperature].

PROTECT FROM LIGHT.

Retain vial in carton until contents are used.

www.fresenius-kabi.us

45842G

Revised: November 2016

PACKAGE LABEL

PACKAGE LABEL - PRINCIPAL DISPLAY - Folic Acid 10 mL Vial Label

Folic Acid Injection, USP

50 mg per 10 mL (5 mg/mL)

For intramuscular, intravenous or subcutaneous use.

10 mL Multiple Dose Vial
Rx only

PACKAGE LABEL - PRINCIPAL DISPLAY - Folic Acid 10 mL Vial Carton Label

Folic Acid Injection, USP

50 mg per 10 mL (5 mg per mL)

For intramuscular, intravenous or subcutaneous use.

10 mL Multiple Dose Vial

Rx only